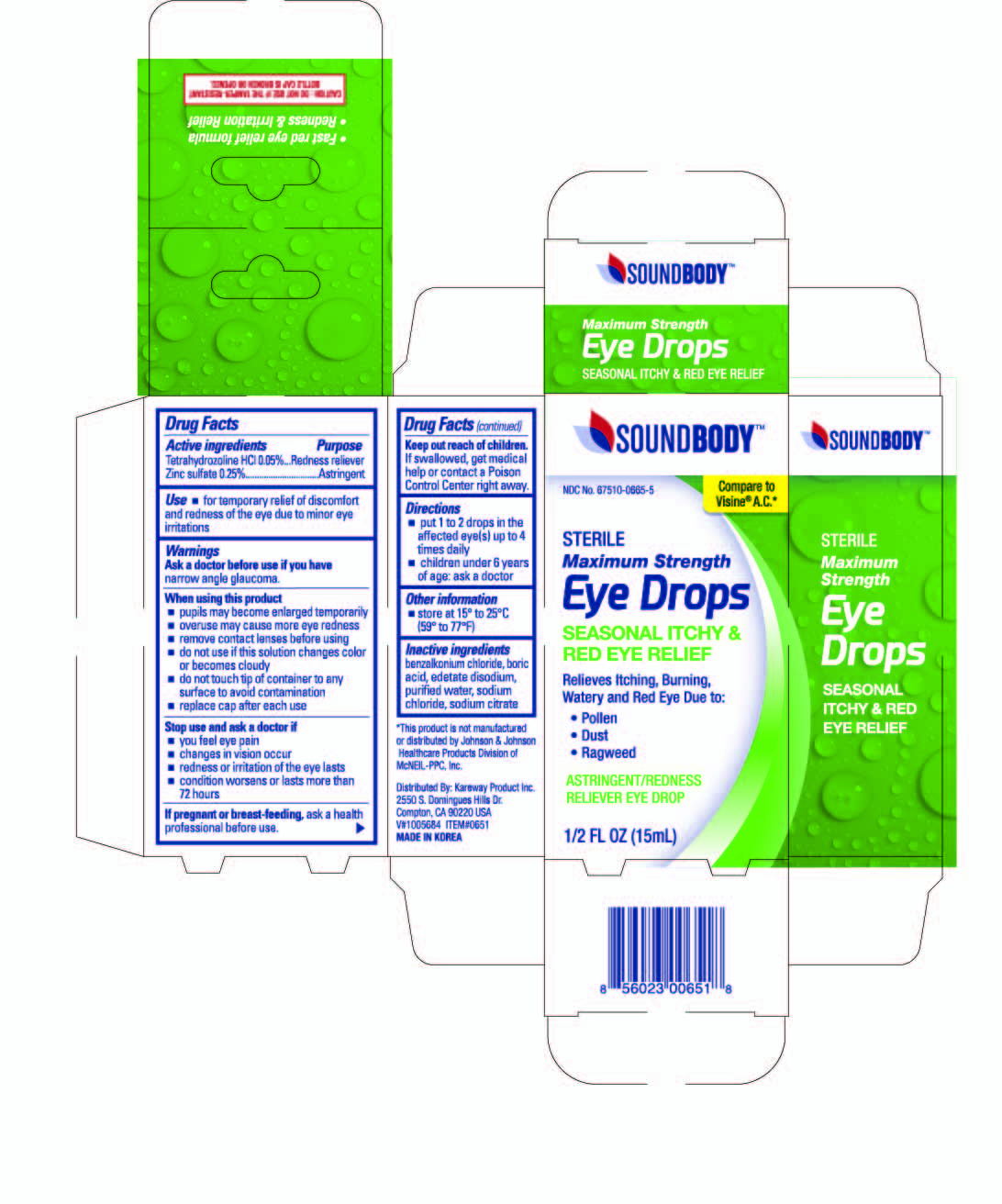 DRUG LABEL: Soundbody Seasonal itchy and Red eye relief
NDC: 67510-0651 | Form: LIQUID
Manufacturer: Kareway Product, Inc.
Category: otc | Type: HUMAN OTC DRUG LABEL
Date: 20220708

ACTIVE INGREDIENTS: TETRAHYDROZOLINE HYDROCHLORIDE 0.05 mg/1 mL; ZINC SULFATE 0.25 mg/1 mL
INACTIVE INGREDIENTS: BENZALKONIUM CHLORIDE; BORIC ACID; EDETATE DISODIUM; SODIUM CITRATE; SODIUM CHLORIDE; WATER

Soundbody Eye drops Seasonal Itchy & Red Eye Relief

Active Ingredient

Tetrahydrozoline HCl 0.05%

Zinc sulfate 0.25%

Purpose

Redness reliever

Astringent

Use

- for temporary relief of discomfort and redness of the eye due to minor eye irritations

Warnings

Ask a doctor before use if you have narrow angle glaucoma.

When using this product

- pupils may become enlarged temporarily
- overuse may cause more eye redness
- remove contact lenses before using
- do not use if this solution changes color or become cloudy
- do not touch tip of container to any surface to avoid contamination
- replace cap after each use

Stop use and ask a doctor if

- you feel eye pain
- changes in vision occur
- redness or irritation of the eye lasts
- condition worsens or lasts more than 72 hours

If pregnant or breast-feeding,

ask a health professional before use.

Keep out of reach of children.

If swallowed, get medical help or contact a Poison Control Center right away.

Directions

- put 1 to 2 drops in the affected eye(s) up to 4 times daily
- children under 6 years of age: ask a doctor

Other information

- store at 15° to 25°C (59° to 77°F)

Inactive ingredients

benzalkonium chloride, boric acid, edetate disodium, purified water, sodium chloride, sodium citrate

package label

Soundbody Eye Drops Seasonal Itchy & Red Eye Relief